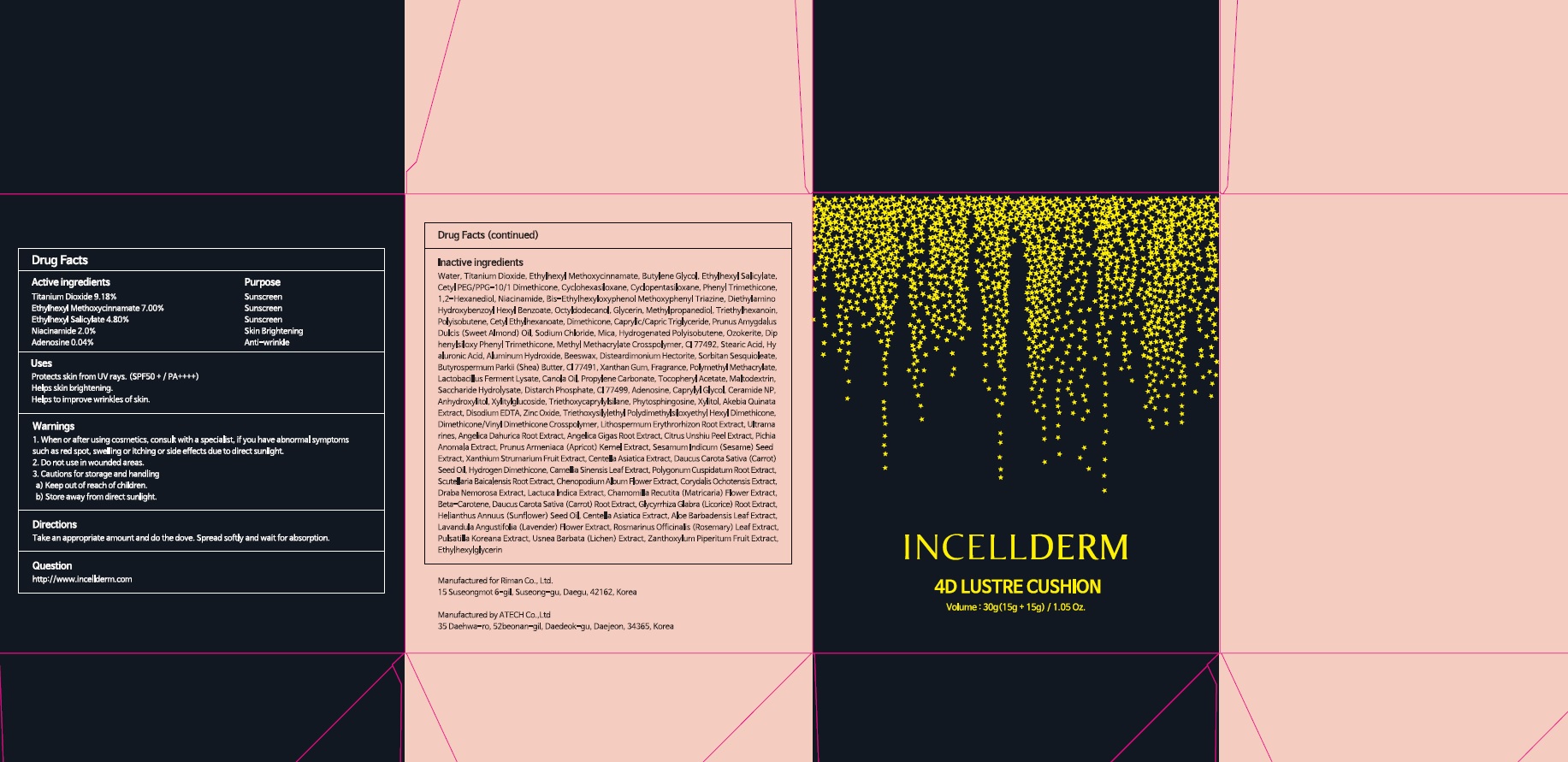 DRUG LABEL: INCELLDERM 4D LUSTRE CUSHION
NDC: 72650-070 | Form: POWDER
Manufacturer: Riman Co., Ltd.
Category: otc | Type: HUMAN OTC DRUG LABEL
Date: 20200610

ACTIVE INGREDIENTS: Titanium Dioxide 1.37 g/15 g; Octinoxate 1.05 g/15 g; Octisalate 0.72 g/15 g; Niacinamide 0.30 g/15 g; Adenosine 0.006 g/15 g
INACTIVE INGREDIENTS: Water; Butylene Glycol

ACTIVE INGREDIENTS

Titanium Dioxide 9.18%
Ethylhexyl Methoxycinnamate 7.00%
Ethylhexyl Salicylate 4.80%
Niacinamide 2.0%
Adenosine 0.04%

INACTIVE INGREDIENTS

Water, Butylene Glycol, Cetyl PEG/PPG-10/1 Dimethicone, Cyclohexasiloxane, Cyclopentasiloxane, Phenyl Trimethicone, 1,2-Hexanediol, Bis-Ethylhexyloxyphenol Methoxyphenyl Triazine, Diethylamino Hydroxybenzoyl Hexyl Benzoate, Octyldodecanol, Glycerin, Methylpropanediol, Triethylhexanoin, Polyisobutene, Cetyl Ethylhexanoate, Dimethicone, Caprylic/Capric Triglyceride, Prunus Amygdalus Dulcis (Sweet Almond) Oil, Sodium Chloride, Mica, Hydrogenated Polyisobutene, Ozokerite, Diphenylsiloxy Phenyl Trimethicone, Methyl Methacrylate Crosspolymer, CI 77492, Stearic Acid, Hyaluronic Acid, Aluminum Hydroxide, Beeswax, Disteardimonium Hectorite, Sorbitan Sesquioleate, Butyrospermum Parkii (Shea) Butter, CI 77491, Xanthan Gum, Fragrance, Polymethyl Methacrylate, Lactobacillus Ferment Lysate, Canola Oil, Propylene Carbonate, Tocopheryl Acetate, Maltodextrin, Saccharide Hydrolysate, Distarch Phosphate, CI 77499, Caprylyl Glycol, Ceramide NP, Anhydroxylitol, Xylitylglucoside, Triethoxycaprylylsilane, Phytosphingosine, Xylitol, Akebia Quinata Extract, Disodium EDTA, Zinc Oxide, Triethoxysilylethyl Polydimethylsiloxyethyl Hexyl Dimethicone, Dimethicone/Vinyl Dimethicone Crosspolymer, Lithospermum Erythrorhizon Root Extract, Ultramarines, Angelica Dahurica Root Extract, Angelica Gigas Root Extract, Citrus Unshiu Peel Extract, Pichia Anomala Extract, Prunus Armeniaca (Apricot) Kernel Extract, Sesamum Indicum (Sesame) Seed Extract, Xanthium Strumarium Fruit Extract, Centella Asiatica Extract, Daucus Carota Sativa (Carrot) Seed Oil, Hydrogen Dimethicone, Camellia Sinensis Leaf Extract, Polygonum Cuspidatum Root Extract, Scutellaria Baicalensis Root Extract, Chenopodium Album Flower Extract, Corydalis Ochotensis Extract, Draba Nemorosa Extract, Lactuca Indica Extract, Chamomilla Recutita (Matricaria) Flower Extract, Beta-Carotene, Daucus Carota Sativa (Carrot) Root Extract, Glycyrrhiza Glabra (Licorice) Root Extract, Helianthus Annuus (Sunflower) Seed Oil, Centella Asiatica Extract, Aloe Barbadensis Leaf Extract, Lavandula Angustifolia (Lavender) Flower Extract, Rosmarinus Officinalis (Rosemary) Leaf Extract, Pulsatilla Koreana Extract, Usnea Barbata (Lichen) Extract, Zanthoxylum Piperitum Fruit Extract, Ethylhexylglycerin

PURPOSE

Sunscreen, Skin Brightening, Anti-wrinkle

WARNINGS

1. When or after using cosmetics, consult with a specialist, if you have abnormal symptoms such as red spot, swelling or itching or side effects due to direct sunlight.
2. Do not use in wounded areas.
3. Cautions for storage and handling a) Keep out of reach of children. b) Store away from direct sunlight.

KEEP OUT OF REACH OF CHILDREN

Uses

Protects skin from UV rays. (SPF50 + / PA++++)
Helps skin brightening.
Helps to improve wrinkles of skin.

Directions

Take an appropriate amount and do the dove. Spread softly and wait for absorption.

Questions

http://www.incellderm.com